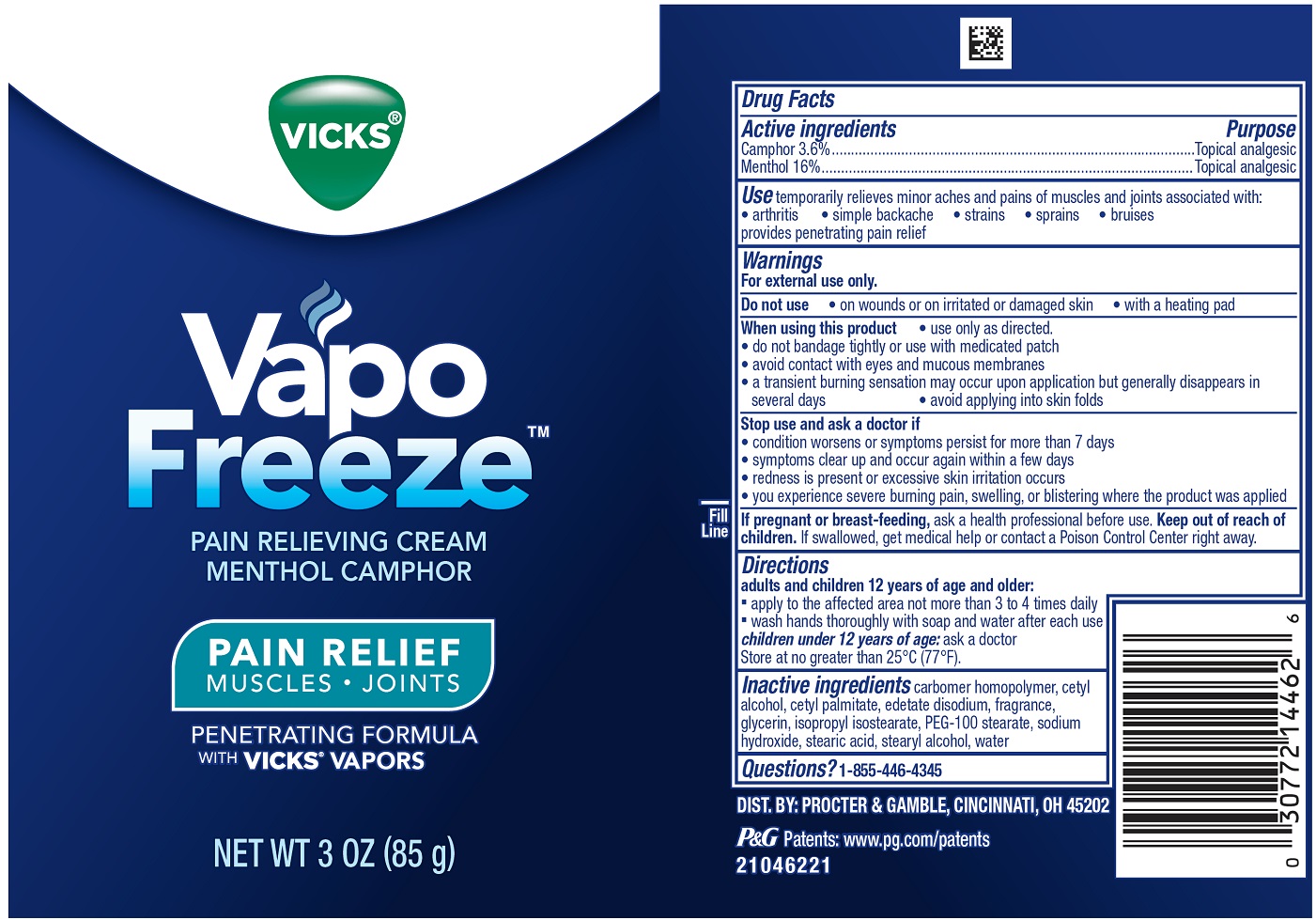 DRUG LABEL: Vicks VapoFreeze
NDC: 84126-302 | Form: CREAM
Manufacturer: The Procter & Gamble Manufacturing Company
Category: otc | Type: HUMAN OTC DRUG LABEL
Date: 20251003

ACTIVE INGREDIENTS: MENTHOL 0.16 g/1 g; CAMPHOR (SYNTHETIC) 0.036 g/1 g
INACTIVE INGREDIENTS: WATER; GLYCERIN; STEARYL ALCOHOL; CARBOMER HOMOPOLYMER TYPE C (ALLYL PENTAERYTHRITOL CROSSLINKED); SODIUM HYDROXIDE; CETYL ALCOHOL; ISOPROPYL ISOSTEARATE; CETYL PALMITATE; EDETATE DISODIUM; PEG-100 STEARATE

Vicks® VapoFreeze™ Pain Relieving Cream

Drug Facts

Active ingredients

Camphor 3.6%

Menthol 16%

Active ingredients Purpose

Topical anesthetic

Topical analgesic

Use

temporarily relieves minor pain aches and pains of muscles and joints associated with:

- arthritis
- simple backache
- strains
- sprains
- bruises

provides penetrating pain relief

Warnings

For external use only

Do not use

- on wounds or on irritated or damaged skin
- with a heating pad

When using this product

- use only as directed.
- do not bandage tightly or use with medicated patch
- avoid contact with eyes and mucous membranes
- do not expose the area to local heat or direct sunlight
- a transient burning sensation may occur upon application but generally disappears in several days
- avoid applying into skin folds

Stop use and ask a doctor if

- condition worsens or symptoms persist for more than 7 days
- symptoms clear up and occur again within a few days
- redness is present or excessive skin irritation occurs
- you experience severe burning pain, swelling, or blistering where the product was applied

If pregnant or breast-feeding,

ask a health professional before use.

Keep out of reach of children.

Directions

adults and children over 12 years of age and older:

- apply to the affected area not more than 3 to 4 times daily
- wash hands thoroughly with soap and water after each use

children under 12 years of age:ask a doctor

Store at no greater than 25°C (77°F).

Inactive ingredients

carbomer homopolymer, cetyl alcohol, cetyl palmitate, edetate disodium, fragrance, glycerin, isopropyl isostearate, PEG-100 stearate, sodium hydroxide, stearic acid, stearyl alcohol, water

Questions?

1-855-446-4345

DIST. BY: PROCTER & GAMBLE, CINCINNATI, OH 45202

PRINCIPAL DISPLAY PANEL - 3 OZ

VICKS®

Vapo

Freeze™

PAIN RELIEVING CREAM

MENTHOL CAMPHOR

PAIN RELIEF

MUSCLES • JOINTS

PENETRATING FORMULA

WITHVICKS®VAPORS

NET WT 3 OZ (85 g)